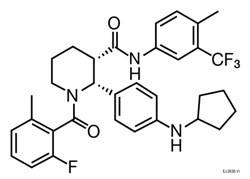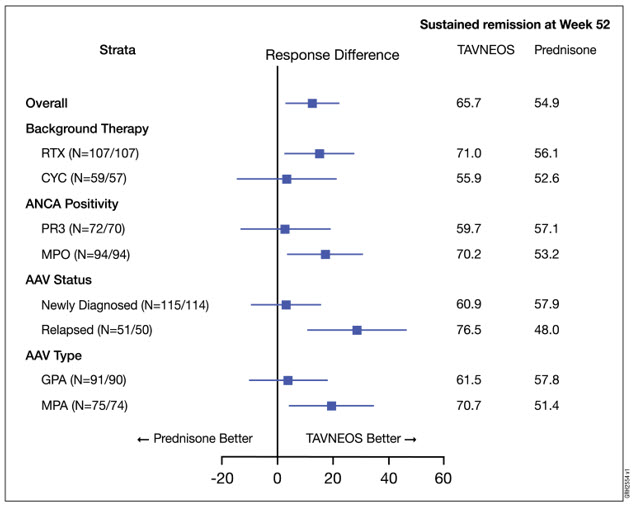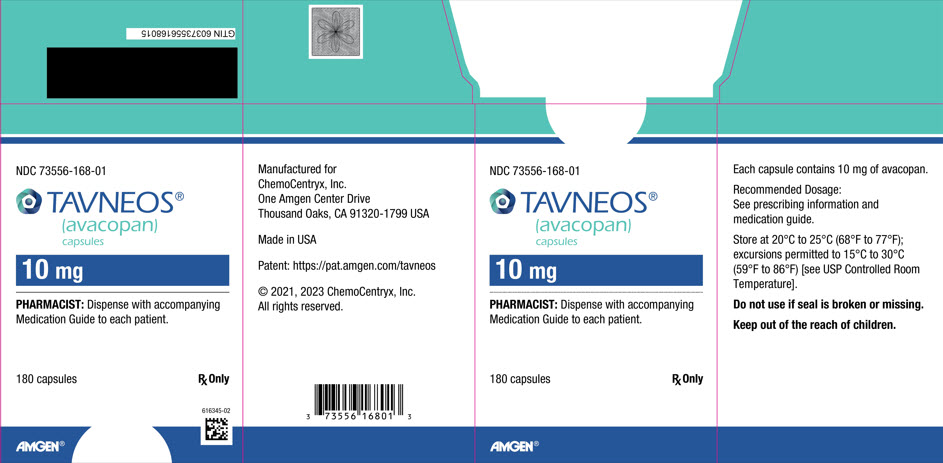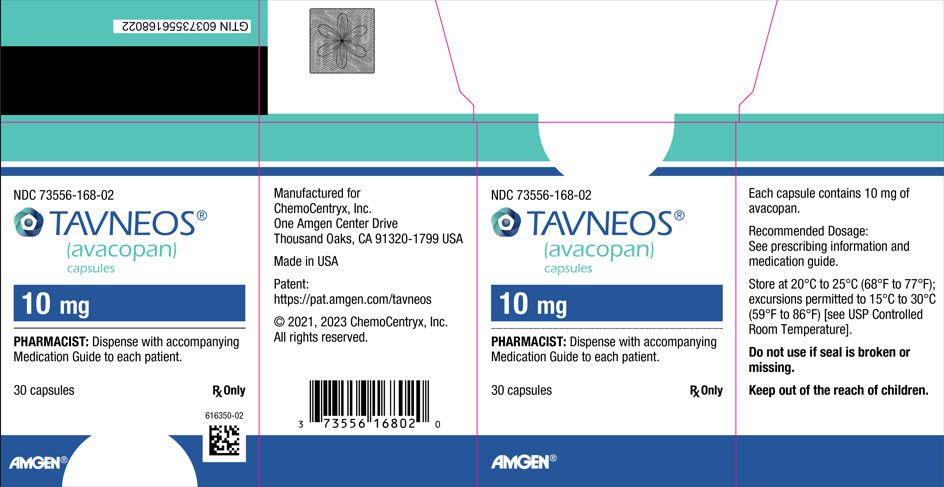 DRUG LABEL: TAVNEOS
NDC: 73556-168 | Form: CAPSULE
Manufacturer: ChemoCentryx, Inc.
Category: prescription | Type: HUMAN PRESCRIPTION DRUG LABEL
Date: 20250618

ACTIVE INGREDIENTS: AVACOPAN 10 mg/1 1
INACTIVE INGREDIENTS: POLYOXYL 40 HYDROGENATED CASTOR OIL; POLYETHYLENE GLYCOL 4000; FERRIC OXIDE RED; FERRIC OXIDE YELLOW; TITANIUM DIOXIDE; GELATIN, UNSPECIFIED; FERROSOFERRIC OXIDE; POLYSORBATE 80

HIGHLIGHTS OF PRESCRIBING INFORMATION

These highlights do not include all the information needed to use TAVNEOS safely and effectively. See full prescribing information for TAVNEOS.
TAVNEOS® (avacopan) capsules, for oral use
Initial U.S. Approval: 2021

1 INDICATIONS AND USAGE

TAVNEOS is a complement 5a receptor (C5aR) antagonist indicated as an adjunctive treatment of adult patients with severe active anti-neutrophil cytoplasmic autoantibody (ANCA)-associated vasculitis (granulomatosis with polyangiitis [GPA] and microscopic polyangiitis [MPA]) in combination with standard therapy including glucocorticoids. TAVNEOS does not eliminate glucocorticoid use. (1)

2 DOSAGE AND ADMINISTRATION

The recommended dosage is 30 mg (three 10 mg capsules) twice daily, with food. (2)

3 DOSAGE FORMS AND STRENGTHS

Capsules: 10 mg (3)

4 CONTRAINDICATIONS

Serious hypersensitivity to avacopan or to any of the excipients. (4)

5 WARNINGS AND PRECAUTIONS

- Hepatotoxicity: Increase in liver function tests occurred in clinical trials. Obtain liver function tests before initiation of therapy and monitor as clinically indicated. (5.1)
- Serious Hypersensitivity Reactions: Cases of angioedema occurred in a clinical trial. Observe for signs and symptoms of angioedema and manage accordingly. (5.2)
- Hepatitis B Virus (HBV) Reactivation: Cases of HBV reactivation occurred in a clinical trial. Withhold TAVNEOS and institute appropriate anti-infective therapy. (5.3)
- Serious Infections: Avoid use of TAVNEOS in patients with active, serious infection, including localized infections. (5.4)

6 ADVERSE REACTIONS

The most common adverse reactions (≥5%) are: nausea, headache, hypertension, diarrhea, vomiting, rash, fatigue, upper abdominal pain, dizziness, blood creatinine increased, and paresthesia.

To report SUSPECTED ADVERSE REACTIONS, contact Amgen Inc. at 1-800-77-AMGEN (1-800-772-6436) or FDA at 1-800-FDA-1088 or www.fda.gov/medwatch.

7 DRUG INTERACTIONS

- Strong and moderate CYP3A4 enzyme inducers: Avoid use. (7.1)
- Strong CYP3A4 enzyme inhibitors: Reduce avacopan dose to 30 mg once daily. (7.2)
- CYP3A4 substrates: Consider dose reduction of CYP3A4 substrates when co-administering TAVNEOS with CYP3A4 substrates. (7.3)

FULL PRESCRIBING INFORMATION

1 INDICATIONS AND USAGE

TAVNEOS is indicated as an adjunctive treatment of adult patients with severe active anti-neutrophil cytoplasmic autoantibody (ANCA)-associated vasculitis (granulomatosis with polyangiitis [GPA] and microscopic polyangiitis [MPA]) in combination with standard therapy including glucocorticoids. TAVNEOS does not eliminate glucocorticoid use.

2 DOSAGE AND ADMINISTRATION

2.1 Recommended Evaluations Prior to Treatment Initiation

Before initiating TAVNEOS, perform the following evaluations:

- Liver Function Tests: Obtain liver test panel (serum alanine aminotransferase [ALT], aspartate aminotransferase [AST], alkaline phosphatase, and total bilirubin) before initiating TAVNEOS. TAVNEOS is not recommended for use in patients with cirrhosis, especially those with severe hepatic impairment (Child-Pugh C) [see Warnings and Precautions (5.1) and Use in Specific Populations (8.7)].
- Hepatitis B (HBV) Serology: Screen patients for HBV infection by measuring HBsAg and anti-HBc. For patients with evidence of prior or current HBV infection, consult with a physician with expertise in managing hepatitis B regarding monitoring and consideration for HBV antiviral therapy before or during treatment with TAVNEOS [see Warnings and Precautions (5.3)].

2.2 Recommended Dosage and Administration

The recommended dose of TAVNEOS is 30 mg (three 10 mg capsules) twice daily, with food.

Advise patients that TAVNEOS capsules should not be crushed, chewed or opened.

If a dose is missed, instruct the patient to wait until the usual scheduled time to take the next regular dose. Instruct the patient not to double the next dose.

2.3 Dosage Modifications Due to CYP3A4 Inhibitors

Reduce the dosage of TAVNEOS to 30 mg once daily when used concomitantly with strong CYP3A4 inhibitors.

3 DOSAGE FORMS AND STRENGTHS

Capsules: 10 mg, opaque, yellow and light orange with CCX168 printed in black.

4 CONTRAINDICATIONS

TAVNEOS is contraindicated in patients with serious hypersensitivity reaction to avacopan or to any of the excipients [see Warnings and Precautions (5.2)].

5 WARNINGS AND PRECAUTIONS

5.1 Hepatotoxicity

Serious cases of hepatic injury have been observed in patients taking TAVNEOS. During controlled trials, the TAVNEOS treatment group had a higher incidence of transaminase elevations and hepatobiliary events, including serious and life-threatening events [see Adverse Reactions 6.1].

Obtain liver test panel (serum alanine aminotransferase [ALT], aspartate aminotransferase [AST], alkaline phosphatase, and total bilirubin) before initiating TAVNEOS, every 4 weeks after start of therapy for the first 6 months of treatment and as clinically indicated thereafter.

If a patient receiving treatment with TAVNEOS presents with an elevation in ALT or AST to >3 times the upper limit of normal, evaluate promptly and consider pausing treatment as clinically indicated.

If AST or ALT is >5 times the upper limit of normal, or if a patient develops transaminases >3 times the upper limit of normal with elevation of bilirubin to >2 times the upper limit of normal, discontinue TAVNEOS until TAVNEOS-induced liver injury is ruled out [see Adverse Reactions (6.1)].

TAVNEOS is not recommended for patients with active, untreated and/or uncontrolled chronic liver disease (e.g., chronic active hepatitis B, untreated hepatitis C, uncontrolled autoimmune hepatitis) and cirrhosis. Consider the risk and benefit before administering TAVNEOS to a patient with liver disease. Monitor patients closely for hepatic adverse reactions [see Use in Specific Populations (8.7)].

5.2 Hypersensitivity Reactions

TAVNEOS may cause angioedema [see Adverse Reactions (6.1)]. In clinical trials, two cases of angioedema occurred, including one serious event requiring hospitalization. If angioedema occurs, discontinue TAVNEOS immediately, provide appropriate therapy, and monitor for airway compromise. TAVNEOS must not be re-administered unless another cause has been established. Educate patients on recognizing the signs and symptoms of a hypersensitivity reaction and to seek immediate medical care should they develop.

5.3 Hepatitis B Virus (HBV) Reactivation

Hepatitis B virus (HBV) reactivation, including life threatening hepatitis B, was observed in the clinical program.

HBV reactivation is defined as an abrupt increase in HBV replication, manifesting as a rapid increase in serum HBV DNA levels or detection of HBsAg, in a person who was previously HBsAg negative and anti-HBc positive. Reactivation of HBV replication is often followed by hepatitis, i.e., increase in transaminase levels. In severe cases, increase in bilirubin levels, liver failure, and death can occur.

Screen patients for HBV infection by measuring HBsAg and anti-HBc before initiating treatment with TAVNEOS. For patients who show evidence of prior hepatitis B infection (HBsAg positive [regardless of antibody status] or HBsAg negative but anti-HBc positive), consult physicians with expertise in managing hepatitis B regarding monitoring and consideration for HBV antiviral therapy before and/or during TAVNEOS treatment.

Monitor patients with evidence of current or prior HBV infection for clinical and laboratory signs of hepatitis, or HBV reactivation during and for six months following TAVNEOS therapy.

In patients who develop reactivation of HBV while on TAVNEOS, immediately discontinue TAVNEOS and any concomitant therapy associated with HBV reactivation, and institute appropriate treatment. Insufficient data exist regarding the safety of resuming TAVNEOS treatment in patients who develop HBV reactivation. Resumption of TAVNEOS treatment in patients whose HBV reactivation resolves should be discussed with physicians with expertise in managing HBV.

5.4 Serious Infections

Serious infections, including fatal infections, have been reported in patients receiving TAVNEOS. The most common serious infections reported in the TAVNEOS group were pneumonia and urinary tract infections.

Avoid use of TAVNEOS in patients with an active, serious infection, including localized infections. Consider the risks and benefits of treatment prior to initiating TAVNEOS in patients:

- with chronic or recurrent infection
- who have been exposed to tuberculosis
- with a history of a serious or an opportunistic infection
- who have resided or traveled in areas of endemic tuberculosis or endemic mycoses; or
- with underlying conditions that may predispose them to infection.

Closely monitor patients for the development of signs and symptoms of infection during and after treatment with TAVNEOS. Interrupt TAVNEOS if a patient develops a serious or opportunistic infection. A patient who develops a new infection during treatment with TAVNEOS should undergo prompt and complete diagnostic testing appropriate for an immunocompromised patient; appropriate antimicrobial therapy should be initiated, the patient should be closely monitored, and TAVNEOS should be interrupted if the patient is not responding to antimicrobial therapy. TAVNEOS may be resumed once the infection is controlled.

6 ADVERSE REACTIONS

The following adverse reactions are discussed in greater detail in other sections of the labeling:

- Hepatotoxicity [see Warnings and Precautions (5.1)]
- Hypersensitivity Reactions [see Warnings and Precautions (5.2)]
- Hepatitis B Virus (HBV) Reactivation [see Warnings and Precautions (5.3)]
- Serious Infections [see Warnings and Precautions (5.4)]

6.1 Clinical Trials Experience

Because the clinical trials are conducted under widely varying conditions, adverse reaction rates observed in the clinical trials of a drug cannot be directly compared with rates in the clinical trials of another drug and may not reflect the rates observed in practice.

The identification of potential adverse drug reactions was based on safety data from the phase 3 clinical trial in which 330 patients with ANCA-associated vasculitis were randomized 1:1 to either TAVNEOS or prednisone [see Clinical Studies (14)]. The mean age of patients was 60.9 years (range of 13 to 88 years), with a predominance of men (56.4%) and Caucasians (84.2%). The cumulative exposure to TAVNEOS was 138.7 patient-years. Additionally, two phase 2 trials were conducted in ANCA-associated vasculitis. The cumulative clinical trial exposure from the phase 2 and 3 trials equals 212.3 patient-years.

The most frequent serious adverse reactions reported more frequently in patients treated with TAVNEOS than with prednisone were pneumonia (4.8% TAVNEOS vs. 3.7% prednisone), GPA (3.0% TAVNEOS vs. 0.6% prednisone), acute kidney injury (1.8% TAVNEOS vs. 0.6% prednisone), and urinary tract infection (1.8% TAVNEOS vs. 1.2% prednisone). Within 52 weeks, 4 patients in the prednisone treatment group (2.4%) and 2 patients in the TAVNEOS group (1.2%) died. There were no deaths in the phase 2 trials.

In the phase 3 trial, seven patients (4.2%) in the TAVNEOS treatment group and 2 patients (1.2%) in the prednisone treatment group discontinued treatment due to hepatic-related adverse reactions, including hepatobiliary adverse reactions and liver enzymes abnormalities. The most frequent adverse reaction that led to drug discontinuation reported by > 1 patient and more frequently reported in patients treated with TAVNEOS was hepatic function abnormal (1.8%).

The most common adverse reactions that occurred in ≥5% of patients and higher in the TAVNEOS group as compared with the prednisone group are listed in Table 1.

Table 1. Adverse Reactions Reported in ≥5% of Patients and Higher in TAVNEOS Group vs. Prednisone Group in Phase 3 Trial
Adverse Reaction | Prednisone (N = 164) n (%) | TAVNEOS (N = 166) n (%)
Nausea | 34 (20.7) | 39 (23.5)
Headache | 23 (14.0) | 34 (20.5)
Hypertension | 29 (17.7) | 30 (18.1)
Diarrhea | 24 (14.6) | 25 (15.1)
Vomiting | 21 (12.8) | 25 (15.1)
Rash | 13 (7.9) | 19 (11.4)
Fatigue | 15 (9.1) | 17 (10.2)
Upper abdominal pain | 10 (6.1) | 11 (6.6)
Dizziness | 10 (6.1) | 11 (6.6)
Blood creatinine increased | 8 (4.9) | 10 (6.0)
Paresthesia | 7 (4.3) | 9 (5.4)
N = number of patients randomized to treatment group in the Safety Population; n = number of patients in specified category.

Hepatotoxicity and Elevated Liver Function Tests

In the phase 3 trial, a total of 19 patients (11.6%) in the prednisone group and 22 patients (13.3%) in the TAVNEOS group had hepatic-related adverse reactions, including hepatobiliary adverse reactions and liver enzyme abnormalities. Study medication was paused or discontinued permanently due to hepatic-related adverse reactions in 5 patients (3.0%) in the prednisone group and 9 patients (5.4%) in the TAVNEOS group. Serious hepatic-related adverse reactions were reported in 6 patients (3.7%) in the prednisone group and 9 patients (5.4%) in the TAVNEOS group. A serious hepatic-related adverse reaction was reported in 1 patient in the TAVNEOS group in the phase 2 studies.

Angioedema

In the phase 3 trial, 2 patients (1.2%) in the TAVNEOS group had angioedema; one event was a serious adverse reaction requiring hospitalization.

Elevated Creatine Phosphokinase

In the phase 3 trial, 1 patient (0.6%) in the prednisone group and 6 patients (3.6%) in the TAVNEOS group had increased creatine phosphokinase. One TAVNEOS-treated patient discontinued treatment due to increased creatine phosphokinase.

7 DRUG INTERACTIONS

7.1 CYP3A4 Inducers

Avacopan exposure is decreased when co-administered with strong CYP3A4 enzyme inducers such as rifampin [see Clinical Pharmacology (12.3)]. Avoid coadministration of strong and moderate CYP3A4 inducers with TAVNEOS.

7.2 CYP3A4 Inhibitors

Avacopan exposure is increased when co-administered with strong CYP3A4 enzyme inhibitors such as itraconazole [see Clinical Pharmacology (12.3)]. Administer TAVNEOS 30 mg once daily when coadministered with strong CYP3A4 inhibitors.

7.3 CYP3A4 Substrates

Avacopan is a moderate CYP3A4 inhibitor. Co-administration of avacopan and 40 mg simvastatin increases the systemic exposure of simvastatin. While taking TAVNEOS, limit simvastatin dosage to 10 mg daily (or 20 mg daily for patients who have previously tolerated simvastatin 80 mg daily for at least one year without evidence of muscle toxicity). Consider dose reduction of CYP3A4 substrates when co-administering TAVNEOS with CYP3A4 substrates. Consult the concomitant CYP3A4 substrate product information when considering administration of such products together with TAVNEOS [see Clinical Pharmacology (12.3)].

8 USE IN SPECIFIC POPULATIONS

8.1 Pregnancy

Risk Summary

There are no adequate and well-controlled studies with TAVNEOS in pregnant women to inform a drug-associated risk. In animal reproduction studies, oral administration of avacopan to pregnant hamsters and rabbits during the period of organogenesis produced no evidence of fetal harm with exposures up to approximately 5 and 0.6 times, respectively, the exposure at the maximum recommended human dose (MRHD) of 30 mg twice daily (on an area under the curve [AUC] basis). Avacopan caused an increase in the number of abortions in rabbits at an exposure 0.6 times the MRHD (see Animal Data).

The background risk of major birth defects and miscarriage for the indicated population are unknown. In the U.S. general population, the estimated background risk of major birth defects and miscarriage in clinically recognized pregnancies is 2-4% and 15-20%, respectively.

Data

Animal Data

In an embryo-fetal development study with pregnant hamsters dosed by the oral route during the period of organogenesis from gestation days 6 to 12, avacopan produced an increase in the incidence of a skeletal variation, described as supernumerary ribs, at an exposure that was 5 times the MRHD (on an AUC basis with a maternal oral dose of 1000 mg/kg/day). No structural abnormalities were noted with exposures up to 5 times the MRHD (on an AUC basis with maternal oral doses up to 1000 mg/kg/day).

In an embryo-fetal development study with pregnant rabbits dosed by the oral route during the period of organogenesis from gestation days 6 to 18, avacopan caused an increase in the number of abortions at an exposure 0.6 times the MRHD (on an AUC basis with a maternal oral dose of 200 mg/kg/day), however, no evidence of fetal harm was observed with such exposures. Maternal toxicity, as evidenced by decreased body weight gains, was observed at exposures 0.6 times and higher than the MRHD (on an AUC basis with maternal oral doses of 30 mg/kg/day and higher).

In a prenatal and postnatal development study with pregnant hamsters dosed by the oral route during the periods of gestation and lactation from gestation day 6 to lactation day 20, avacopan had no effects on the growth and development of offspring with exposures up to approximately 5 times the MRHD (on an AUC basis with maternal oral doses up to 1000 mg/kg/day).

8.2 Lactation

Risk Summary

There are no available data on the effects of avacopan on the breastfed child or on milk production. It is unknown whether avacopan is secreted in human milk. Avacopan was detected in the plasma of undosed hamster pups nursing from drug-treated dams (see Animal Data). The developmental and health benefits of breastfeeding should be considered along with the mother's clinical need for TAVNEOS and any potential adverse effects on the breast-fed infant from TAVNEOS or from the underlying maternal condition.

Animal Data

Avacopan has not been measured in the milk of lactating animals; however, it was detected in the plasma of nursing offspring in a pre- and post-natal development study with hamsters at a pup to maternal plasma ratio of 0.37. This finding suggests that avacopan is secreted into the milk of lactating hamsters. [see Nonclinical Toxicology (13.1)].

8.4 Pediatric Use

The safety and effectiveness of TAVNEOS in pediatric patients have not been established.

8.5 Geriatric Use

Of the 86 geriatric patients who received TAVNEOS in the phase 3 randomized clinical trial for ANCA-associated vasculitis [see Clinical Studies (14)], 62 patients were between 65-74 years and 24 were 75 years or older. No overall differences in safety or effectiveness were observed between geriatric patients and younger patients.

8.6 Patients with Renal Impairment

No dose adjustment is required for patients with mild, moderate, or severe renal impairment [see Clinical Pharmacology (12.3)]. TAVNEOS has not been studied in patients with ANCA-associated vasculitis who are on dialysis.

8.7 Patients with Hepatic Impairment

No dosage adjustment is recommended for patients with mild or moderate (as indicated by the Child-Pugh method) hepatic impairment [Clinical Pharmacology (12.3)]. TAVNEOS has not been studied in patients with severe hepatic impairment (Child-Pugh Class C).

11 DESCRIPTION

TAVNEOS (avacopan) capsules contain avacopan, a C5aR antagonist. Avacopan is a chiral molecule containing two stereocenters and has a chemical name of (2R,3S)-2-[4-(cyclopentylamino)phenyl]-1-(2-fluoro-6-methylbenzoyl)-N-[4-methyl-3-(trifluoromethyl)phenyl]piperidine-3-carboxamide. It has a molecular formula of C33H35F4N3O2 and a molecular weight of 582 g/mol. Avacopan has the following structural formula:

Avacopan is a white to pale yellow crystalline solid that is soluble in organic solvents and practically insoluble in water.

TAVNEOS is available as a 10 mg capsule for oral administration. The capsules include the following inactive ingredients: Polyethylene glycol 4000 (PEG-4000), Polyoxyl-40 hydrogenated castor oil. The capsules are a light orange and yellow opaque bicolor gelatin capsule with a clear gelatin sealing band. The top half of the capsule is printed with "CCX168" in black ink. The capsule shell contains gelatin, red iron oxide, yellow iron oxide, and titanium dioxide, and the capsule sealing band contains gelatin and polysorbate 80.

12 CLINICAL PHARMACOLOGY

12.1 Mechanism of Action

Avacopan is a complement 5a receptor (C5aR) antagonist that inhibits the interaction between C5aR and the anaphylatoxin C5a. Avacopan blocks C5a-mediated neutrophil activation and migration. The precise mechanism by which avacopan exerts a therapeutic effect in patients with ANCA-associated vasculitis has not been definitively established.

12.2 Pharmacodynamics

Avacopan blocks the C5a-induced upregulation of CD11b (integrin alpha M) on neutrophils taken from humans dosed with avacopan. The clinical significance of the pharmacodynamic effect is unclear.

Cardiac Electrophysiology

At the approved recommended dose, TAVNEOS does not prolong the QT interval to any clinically relevant extent.

12.3 Pharmacokinetics

Based on population pharmacokinetic analysis, the mean steady state plasma exposure estimates of avacopan are 3466 ± 1921 ng∙h/mL for the 12-hour area under the plasma drug concentration over time curve (AUC0-12hr) and 349 ± 169 ng/mL for the maximum plasma concentration (Cmax) in patients with ANCA-associated vasculitis receiving 30 mg avacopan twice daily. Steady state plasma levels of avacopan are reached by 13 weeks and the accumulation is approximately 4-fold.

Absorption

Co-administration of 30 mg in capsule formulation with a high-fat, high-calorie meal increases AUC and Cmax of avacopan by approximately 72% and 8%, respectively, and delays tmax by approximately 4 hours (from 2.0 hours to 6.0 hours).

Distribution

The plasma protein binding (e.g., to albumin and α1-acid glycoprotein) of avacopan and metabolite M1 is greater than 99.9%. The apparent volume of distribution of avacopan is estimated to be 345 L.

Elimination

Based on population pharmacokinetic analysis, the estimated total apparent body clearance (CL/F) of avacopan is 16.3 L/h. Following a single dose of 30 mg avacopan with food, the mean elimination half-lives of avacopan and M1 are 97.6 hours and 55.6 hours, respectively, in healthy subjects.

Metabolism

CYP3A4 is the major enzyme responsible for the clearance of avacopan and for the formation and clearance of the major circulating metabolite M1, a mono-hydroxylated product of avacopan. M1 was present at ~12% of the total drug-related materials in plasma and has approximately the same activity as avacopan on the C5aR.

Excretion

The main route of clearance of avacopan is metabolism followed by biliary excretion of the metabolites into feces. Following oral administration of radiolabelled avacopan, about 77% and 10% of the radioactivity was recovered in feces and urine, respectively, and 7% and <0.1% of the radioactive dose was recovered as unchanged avacopan in feces and urine, respectively.

Specific Populations

No clinically significant differences in plasma exposure of avacopan and metabolite M1 were observed based on race (White, Asian, Black), gender (female 31%), age (18 to 83 years), body weight (40.3-174 kg), and renal function (eGFR 14-170 mL/min/1.73 m^2 at baseline).

Patients with Hepatic Impairment

Mild (Child-Pugh A) or moderate (Child-Pugh B) hepatic impairment had no clinically relevant effect on avacopan and M1 plasma exposure. In subjects with mild or moderate hepatic impairment, avacopan AUC increased by 12% and 12%, respectively, Cmax decreased by 13% and 17%, respectively, compared to subjects with normal liver function. In subjects with mild or moderate hepatic impairment, M1 AUC increased by 11% and 18%, respectively, Cmax decreased by 5% and 16%, respectively, compared to subjects with normal liver function.

TAVNEOS has not been studied in subjects with severe hepatic impairment (Child-Pugh Class C).

Drug Interaction Studies

Effects of Other Drugs on TAVNEOS

Avacopan is primarily metabolized by CYP3A4. In vitro studies indicate that avacopan is not a substrate of BCRP and P-gp efflux, and OATP1B1 and OATP1B3 uptake transporters. M1 is a substrate of P-gp but is not a substrate of BCRP efflux, and OATP1B1 and OATP1B3 uptake transporters. Summary of results from a clinical study which evaluated the effect of co-administered drugs on avacopan and M1 plasma exposures is shown in Table 2.

Table 2. Changes in Pharmacokinetics of Avacopan and M1 in the Presence of Co-administered Drugs
Co-administered Drug | Regimen of Co-administered Drug | Ratio (90% CI) [Ratios for Cmax and AUC comparing co-administration of the medication with avacopan vs. administration of avacopan alone.]
Co-administered Drug | Regimen of Co-administered Drug |  | Cmax | AUC
Strong CYP3A4 inhibitor: itraconazole | 200 mg once daily for 4 days | Avacopan | 1.87 (1.70, 2.06) | 2.19 (2.00, 2.41)
Strong CYP3A4 inhibitor: itraconazole | 200 mg once daily for 4 days | M1 | 1.03 (0.95, 1.11) | 1.19 (1.11, 1.28)
Strong CYP3A4 inducer: rifampin | 600 mg once daily for 11 days | Avacopan | 0.21 (0.18, 0.25) | 0.07 (0.06, 0.10)
Strong CYP3A4 inducer: rifampin | 600 mg once daily for 11 days | M1 | 0.27 (0.23, 0.31) | 0.07 (0.06, 0.09)
CI: Confidence interval

Proton-pump inhibitors such as omeprazole are not expected to have a clinically relevant effect on avacopan plasma exposure.

Effect of TAVNEOS on Other Drug Substances

In vitro studies indicate that avacopan does not inhibit CYP1A2, CYP2B6, CYP2C8, CYP2C9, CYP2C19, and CYP2D6, and does not induce CYP1A2 and CYP2B6, but shows induction and time-dependent inhibition of CYP3A4. In vitro studies indicate that M1 does not inhibit CYP1A2, CYP2B6, CYP2C8, CYP2C19, and CYP2D6, and has a low potential to induce CYP3A4, CYP1A2 and CYP2B6, but may inhibit CYP2C9 and CYP3A4.

In vitro studies indicate that avacopan and M1 do not inhibit the transporters P-gp, BCRP, OATP1B1, OATP1B3, OCT2, OAT1, OAT3, MATE1, and MATE2K at clinically relevant concentrations.

Summary of results from clinical studies which evaluated the effect of avacopan on other drugs is shown in Table 3.

Table 3. Change in Pharmacokinetics of Co-administered Drugs in the Presence of Avacopan
Co-administered Drug | Regimen of Avacopan | Ratio (90% CI) [Ratios for Cmax and AUC comparing co-administration of the medication with avacopan vs. administration of medication alone.]
Co-administered Drug | Regimen of Avacopan | Cmax | AUC
Sensitive CYP3A4 substrate: simvastatin | 60 mg twice daily for 7 days (fed) [Avacopan doses were taken with food. Avacopan systemic exposure represents the therapeutic exposure at steady state with 30 mg twice daily under fed conditions.] | 3.20 (2.49, 4.10) | 3.53 (3.23, 3.85)
Sensitive CYP3A4 substrate: midazolam | 30 mg twice daily for 11 days (fasted) [Avacopan doses were taken under fasted conditions. No food was allowed for at least 2 hours post dose for the morning doses. Avacopan systemic exposure was below the therapeutic exposure at steady state with 30 mg twice daily under fed conditions.] | 1.55 (1.41, 1.69) | 1.81 (1.65, 1.98)
Sensitive CYP2C9 substrate: celecoxib | 30 mg twice daily for 11 days (fasted) | 1.64 (1.34, 2.00) | 1.15 (1.03, 1.28)
CI: Confidence interval

13 NONCLINICAL TOXICOLOGY

13.1 Carcinogenesis, Mutagenesis, Impairment of Fertility

Carcinogenesis

Two-year carcinogenicity studies in Sprague-Dawley rats and Syrian hamsters were conducted to assess the carcinogenic potential of avacopan. Avacopan demonstrated no tumorigenic potential in a study with rats that received oral doses up to 100 mg/kg/day (approximately 3 times the MRHD in adults on an AUC basis) and a study in hamsters that received oral doses up to 100 mg/kg/day (approximately 6 times the MRHD in adults on an AUC basis).

Mutagenesis

Avacopan was not mutagenic or clastogenic in the following assays: in vitro bacterial reverse mutation (Ames) test, in vitro mouse lymphoma assay, and in vivo rat micronucleus test.

Impairment of Fertility

Fertility and reproductive performance were unaffected in male and female hamsters that received avacopan by the oral route at dose levels up to 1000 mg/kg/day (approximately 7 times the MRHD on an AUC basis).

14 CLINICAL STUDIES

The efficacy and safety of TAVNEOS was evaluated in a double-blind, active-controlled, phase 3 clinical trial (NCT02994927) in 330 patients with newly diagnosed or relapsed ANCA-associated vasculitis who were randomized 1:1 to one of the following treatment groups:

1. TAVNEOS group (N = 166): Patients received 30 mg avacopan twice daily for 52 weeks plus prednisone-matching placebo for 20 weeks
2. Prednisone group (N = 164): Patients received avacopan-matched placebo twice daily for 52 weeks plus prednisone (tapered from 60 mg/day to 0 over 20 weeks)

All patients in both groups received one of the following standard immunosuppressive regimens:

- IV cyclophosphamide 15 mg/kg IV up to 1.2 g maximum every 2 to 3 weeks for 13 weeks followed by oral azathioprine 1 mg/kg/day with titration up to 2 mg/kg/day (or mycophenolate mofetil at a target dose of 2 g/day if azathioprine was contraindicated) from Week 15 onwards
- Oral cyclophosphamide 2 mg/kg/day (maximum 200 mg/day) for 14 weeks followed by azathioprine 1 mg/kg/day with titration up to 2 mg/kg/day (or mycophenolate mofetil at a target dose of 2 g/day if azathioprine was contraindicated) from Week 15 onwards
- IV rituximab 375 mg/m^2 once weekly for 4 weeks without azathioprine or mycophenolate mofetil

Glucocorticoids were allowed as pre-medication for rituximab to reduce hypersensitivity reactions, taper after glucocorticoids given during the Screening period, treatment of persistent vasculitis, worsening of vasculitis, or relapses, as well as for non-vasculitis reasons such as adrenal insufficiency.

Randomization was stratified based on 3 factors: newly-diagnosed or relapsing ANCA-associated vasculitis, proteinase 3 positive or myeloperoxidase positive ANCA-associated vasculitis, and standard immunosuppressive regimen. The primary endpoints of the study were disease remission at Week 26 and sustained disease remission at Week 52. Disease remission was defined as achieving a Birmingham Vasculitis Activity Score (BVAS) of 0 and no use of glucocorticoids for treatment of ANCA-associated vasculitis from Week 22 to Week 26. Sustained remission was defined as remission at Week 26 and remission at Week 52, without relapse between Week 26 and Week 52. Remission at Week 52 was defined as BVAS of 0 and no use of glucocorticoids for treatment of ANCA-associated vasculitis from Week 48 to Week 52. Relapse was defined as occurrence of one major item, at least 3 non-major items, or 1 or 2 non-major items for at least 2 consecutive visits on the BVAS after remission (BVAS of 0) had been achieved.

The two treatment groups were well balanced regarding baseline demographics and disease characteristics of patients in this trial. The mean patient age was 60.9 years. Most patients were male (56.4%), Caucasian (84.2%), and had newly diagnosed disease (69.4%). Patients had either GPA (54.8%) or MPA (45.2%) and had presence of anti-PR3 (43.0%) or anti-MPO (57.0%) antibodies. Mean baseline BVAS was 16.2; patients most commonly had manifestations within the renal component (81.2%), general component (68.2%), ear/nose/throat component (43.6%), and chest component (43.0%). Approximately 65% of patients received rituximab, 31% received IV cyclophosphamide, and 4% received oral cyclophosphamide.

Remission at Week 26 and Sustained Remission at Week 52

Remission was achieved by 72.3% of patients in the TAVNEOS group and 70.1% of patients in the prednisone group at Week 26 (treatment difference: 3.4%, 95% CI [-6.0%, 12.8%]). At Week 52, a significantly higher percentage of patients had sustained remission in TAVNEOS group (65.7%) compared to the prednisone group (54.9%), as presented in Table 4.

Table 4. Sustained Remission at Week 52 in Phase 3 Trial (Intent-to-Treat Population)
 | Prednisone (N = 164) n (%) | TAVNEOS (N = 166) n (%) | Estimate of Treatment Difference | P-value [2-sided p-value of Summary Score Test (Agresti 2013)]
Sustained Remission at Week 52 | 90 (54.9%) | 109 (65.7%) | 12.5% [Summary Score estimate of the common difference in remission rates (Agresti 2013) by using inverse-variance stratum weights] | 0.013
95% CI | (46.9, 62.6) [Clopper and Pearson exact CI] | (57.9, 72.8) | (2.6, 22.3) [Miettinen-Nurminen (Score) confidence limits for the common difference in remission rates] | 0.013
CI = confidence interval; N = number of patients in the analysis population for the specified treatment group; n = number of patients with disease remission; % = 100*n/N

In pre-specified subgroup efficacy analyses, sustained remission at 52 weeks in patients was examined based on stratification factors and GPA/MPA disease. The results are displayed in Figure 1 below.

Figure 1. Forest Plot of Sustained Remission at Week 52 Based on Disease Related Variables

AAV = ANCA-associated vasculitis, CYC = cyclophosphamide, GPA = granulomatosis with polyangiitis, MPA = microscopic polyangiitis; MPO = myeloperoxidase positive, PR3 = anti-proteinase 3 positive, and RTX = rituximab. The treatment difference between TAVNEOS and prednisone groups is presented with point estimate and 95% confidence interval using normal approximation. The notation N = XXX/YYY indicates the number of patients randomized who received at least one dose of drug in TAVNEOS arm and prednisone arm, respectively. Subgroup findings should be interpreted with caution due to small sample sizes and overlapping subgroups.

16 HOW SUPPLIED/STORAGE AND HANDLING

TAVNEOS (avacopan) capsule is supplied as a 10 mg, hard, opaque yellow and light orange capsule with "CCX168" printed in black.

- Bottle containing 180 capsules with child resistant induction seal closure (NDC 73556-168-01)
- Bottle containing 30 capsules with child resistant induction seal closure (NDC 73556-168-02)

STORAGE AND HANDLING

Store at 20°C to 25°C (68°F to 77°F); excursions permitted to 15°C to 30°C (59°F to 86°F) [see USP Controlled Room Temperature].

Do not use if seal is broken or missing.

17 PATIENT COUNSELING INFORMATION

Advise the patient to read the FDA-approved patient labeling (Medication Guide).

- Dosage and Administration: Instruct the patient that TAVNEOS should be swallowed whole. TAVNEOS should not be chewed or crushed. If a dose is missed, instruct the patient to take the next scheduled dose [see Dosage and Administration (2.2)].
- Hypersensitivity Reactions: Advise patients to seek immediate medical attention when experiencing any signs or symptoms suggesting angioedema (swelling of face, extremities, eyes, lips, tongue, and difficulty in swallowing or breathing) and to discontinue the drug until they have consulted with the prescribing physician [see Warnings and Precautions (5.2)].
- Hepatotoxicity: Inform patients of the signs and symptoms of hepatic adverse reactions. Advise patients to contact their healthcare provider immediately for signs or symptoms of liver problems; yellowing of the skin or the white part of the eyes (jaundice), dark or brown (tea colored) urine, pain on the upper right side of the stomach area (abdomen), bleeding or bruising [see Warnings and Precautions (5.1)].
- Infections: Inform patients that serious infections have been reported in patients receiving TAVNEOS, including reactivation of hepatitis B infection. Instruct patients to contact their healthcare provider immediately if they develop any signs or symptoms of an infection [see Warnings and Precautions (5.4)].
- Lactation: Consider benefits/risk during lactation [see Use in Specific Populations (8.2)].

TAVNEOS® (avacopan)

Manufactured for:
ChemoCentryx, Inc.
One Amgen Center Drive
Thousand Oaks, CA 91320-1799

Patent: https://pat.amgen.com/tavneos

© 2021, 2024 ChemoCentryx, Inc. All rights reserved.

1xxxxxx – v3

MEDICATION GUIDE
TAVNEOS® (tav' nee ose)
(avacopan)
capsules, for oral use

What is the most important information I should know about TAVNEOS?

TAVNEOS may cause serious side effects, including:

- Liver problems. People taking TAVNEOS may have serious liver problems. Call your healthcare provider right away if you have unexplained symptoms such as:

- yellowing of your skin or the white part of your eyes (jaundice)
- pain on the upper right side of your stomach area (abdomen)
- feeling tired

- dark or brown (tea colored) urine
- bleeding or bruising more easily than normal
- loss of appetite

Your healthcare provider will do blood tests to check how well your liver is working before starting and during your treatment with TAVNEOS.

What is TAVNEOS?

- TAVNEOS is a prescription medicine that is used with other medicines (such as glucocorticoids) to treat adults with severe active anti-neutrophil cytoplasmic autoantibody (ANCA)- associated vasculitis (granulomatosis with polyangiitis [GPA], formerly known as Wegener's granulomatosis, and microscopic polyangiitis [MPA]).

It is not known if TAVNEOS is safe and effective in children under the age of 18.

Do not take TAVNEOS:

- if you are allergic to avacopan or any of the other ingredients in TAVNEOS. See the end of this Medication Guide for a complete list of the ingredients in TAVNEOS.
  - Get medical help right away if you experience swollen lips, tongue, throat, trouble swallowing, or difficulty breathing. These could be signs of an allergic reaction. Do not take more of TAVNEOS until you have consulted with your healthcare provider.

Before taking TAVNEOS, tell your healthcare provider about all your medical conditions including if you:

- have or have had abnormal liver blood tests.
- have or have had liver problems.
- have or think you may have hepatitis B or hepatitis C.
- have an infection.
- are pregnant or are planning to become pregnant. It is not known if TAVNEOS will harm your unborn baby. Talk to your healthcare provider if you are pregnant or plan to become pregnant.
- are breastfeeding or plan to breastfeed. It is not known if TAVNEOS can pass into your breast milk. Talk to your healthcare provider about the best way to feed your baby if you take TAVNEOS.

Tell your healthcare provider about all the other medicines you take, including prescription and over-the-counter medicines, vitamins, and herbal supplements. TAVNEOS and certain other medicines may affect each other and cause side effects. Keep a list of the medicines you take and show it to your healthcare provider and pharmacist.

- Some medicines should not be taken with TAVNEOS.
- Your healthcare provider may prescribe other medicines to treat your disease.

How should I take TAVNEOS?

- Take TAVNEOS exactly as your healthcare provider tells you to take it. Do not stop taking TAVNEOS unless your healthcare provider tells you to.
- Check with your healthcare provider or pharmacist if you are not sure.
- Take 3 capsules of TAVNEOS 2 times daily (morning and evening) with food.
- Your healthcare provider may tell you to take 3 capsules of TAVNEOS 1 time each day if you take certain medicines. Tell your healthcare provider about all the medicines you take.
- Swallow the capsules whole with water. Do not crush, chew or open the capsules.
- If you miss a dose of TAVNEOS, do not take the missed dose. Just take the next dose at your regular time.
  If you have taken too much TAVNEOS, call your doctor or a Poison Control Center, or go to the nearest hospital emergency room.

What are the possible side effects of TAVNEOS?
TAVNEOS may cause serious side effects, including:

- See "What is the most important information I should know about TAVNEOS?"
- Serious allergic reactions. TAVNEOS may cause serious allergic reactions. Stop taking TAVNEOS and get emergency medical help right away if you have any of the following signs of a serious allergic reaction:
  - shortness of breath or trouble breathing
  - swollen lips, tongue, throat, or face
  - trouble swallowing
  - chest pain
  - feeling dizzy or faint
  - moderate or severe abdominal pain or vomiting
- Hepatitis B virus (HBV) reactivation. Before you take TAVNEOS, your healthcare provider will do blood tests to check for hepatitis B (HBV) infection. If you have had hepatitis B or are a carrier of hepatitis B virus, taking TAVNEOS could cause the virus to become an active infection again. Your healthcare provider may decide to stop TAVNEOS and any other medicines if you have active hepatitis B liver disease. Your healthcare provider will tell you if and when you can start taking TAVNEOS again. Your healthcare provider will monitor you for hepatitis B infection during and for six months after you stop taking TAVNEOS. Tell your healthcare provider right away if you get worsening tiredness or yellowing of your skin or white part of your eyes during treatment with TAVNEOS.
- Serious infections. Serious infections can happen in people taking TAVNEOS, and these infections can lead to death. The most common serious infections with TAVNEOS were pneumonia and urinary tract infections. People with serious infections should not take TAVNEOS. Tell your healthcare provider right away if you have any symptoms of infection:
  - fever
  - cold symptoms, such as runny nose or sore throat that do not go away
  - flu symptoms, such as cough, tiredness, and body aches
  - earache or headache
  - pain during urination
  - cold sores in mouth or throat
  - cuts, scrapes, or incisions that are red, warm, swollen, or painful

The most common side effects of TAVNEOS include:

- nausea
- diarrhea
- tiredness
- increase in blood creatinine

- headache
- vomiting
- stomach pain
- burning or prickling sensation

- high blood pressure
- rash
- dizziness

These are not all the possible side effects of TAVNEOS.
Call your doctor for medical advice about side effects. You may report side effects to FDA at 1-800-FDA-1088.

How should I store TAVNEOS?
Store TAVNEOS capsules at room temperature between 68°F to 77°F (20°C to 25°C).
Keep TAVNEOS and all medicines out of reach of children.

General information about the safe and effective use of TAVNEOS.
Medicines are sometimes prescribed for purposes other than those listed in a Medication Guide. Do not use TAVNEOS for a condition for which it was not prescribed. Do not give TAVNEOS to other people, even if they have the same symptoms you have. It may harm them. You can ask your pharmacist or healthcare provider for information that is written for healthcare professionals.

What are the ingredients in TAVNEOS?
Active ingredient: avacopan
Inactive ingredients: Polyethylene glycol 4000 (PEG-4000), Polyoxyl-40 hydrogenated castor oil.

Manufactured for: ChemoCentryx, Inc., One Amgen Center Drive, Thousand Oaks, CA 91320-1799
Patent: https://pat.amgen.com/tavneos
© 2021, 2023 ChemoCentryx, Inc. All rights reserved. 1xxxxxx - v2
For more information, go to www.TAVNEOS.com or call Amgen at 1-800-772-6436.

This Medication Guide has been approved by the U.S. Food and Drug Administration

Revised: 8/2023

PRINCIPAL DISPLAY PANEL - 180 Capsule Bottle Carton

NDC 73556-168-01

TAVNEOS®
(avacopan)
capsules

10 mg

PHARMACIST: Dispense with accompanying
Medication Guide to each patient.

180 capsules
Rx Only

AMGEN®

PRINCIPAL DISPLAY PANEL - 30 Capsule Bottle Carton

NDC 73556-168-02

TAVNEOS®
(avacopan)
capsules

10 mg

PHARMACIST: Dispense with accompanying
Medication Guide to each patient.

30 capsules
Rx Only

AMGEN®